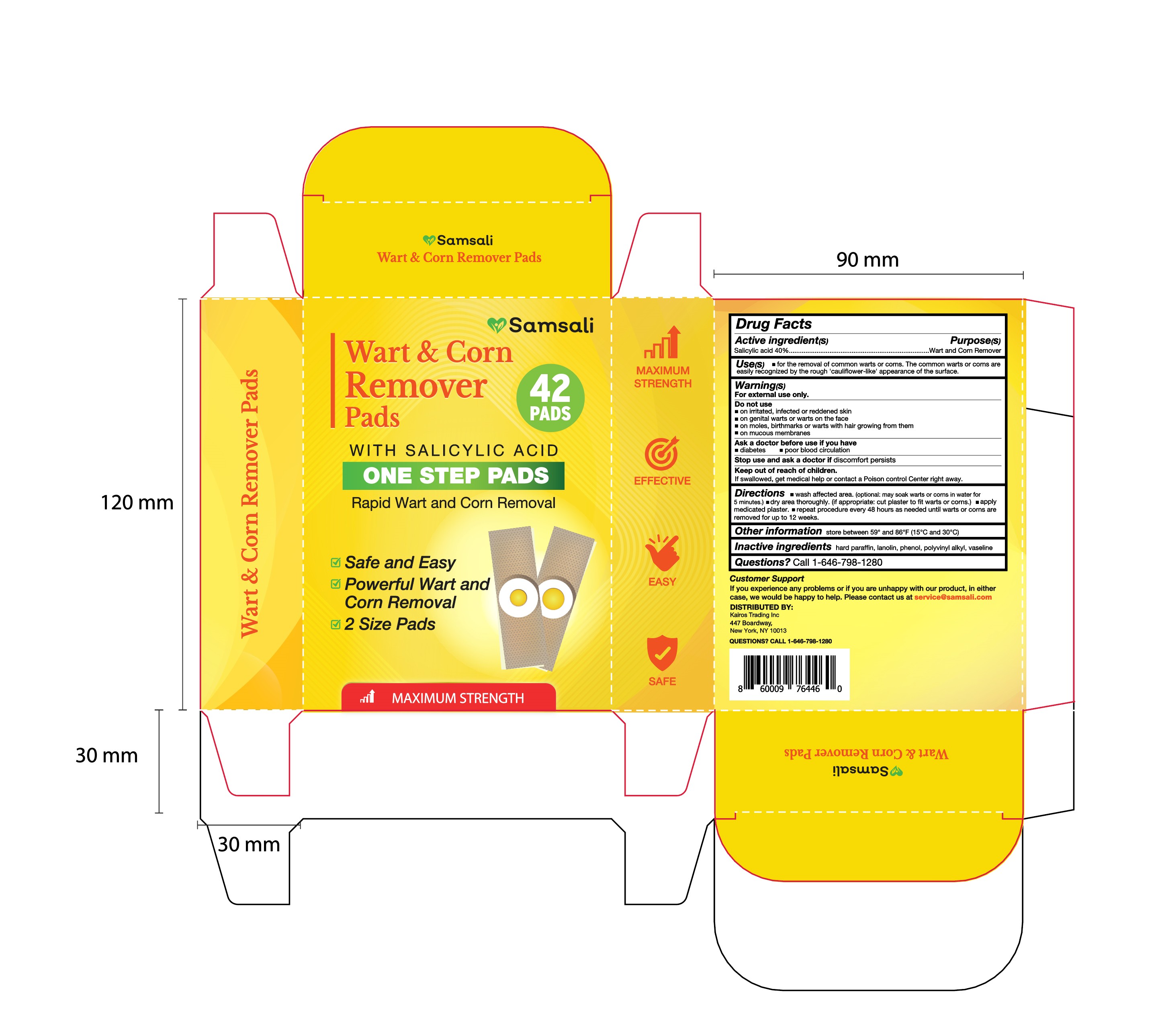 DRUG LABEL: Samsali Wart Corn Remover Pads
NDC: 83818-004 | Form: PATCH
Manufacturer: Shenzhen Xinxin Yunhai Technology Co., Ltd.
Category: otc | Type: HUMAN OTC DRUG LABEL
Date: 20240919

ACTIVE INGREDIENTS: SALICYLIC ACID 40 g/100 1
INACTIVE INGREDIENTS: CLEMATIS VIORNA WHOLE; PARAFFIN; PHENOL; LANOLIN

83818-004-01

Active Ingredient

Salicylic acid 40%

Purpose

Wart and Corn Remover

Use

For the removal of warts and corns.

Warnings

For external use only.

Do not use

On irritated, infected, or reddened skin; on genital warts or warts on the face; on moles, birthmarks, or warts with hair growing from them; on mucous membranes.

When Using

Avoid eye or face contact. If the product gets into eyes or faces, thoroughly rinse with water.

Stop Use

Discomfort persists

Ask Doctor

Diabetes; Poor blood circulation

Keep Oot Of Reach Of Children

If swallowed, get medical help or contact a Poison control Center right away.

Directions

wash affected area.(optional: may soak wart in warm water for 5 minutes.); dry area thoroughly. (if appropriate: cut plaster to fit wart.); apply medicated plaster; repeat procedure every 48 hours as needed until wart is removed for up to 12 weeks;

Other information

store between 59° and 86°F (15°C and 30°C)

Inactive ingredients

hard paraffin, lanolin, phenol, polyvinyl alkyl, vaseline

Questions

Call 1-646-798-1280